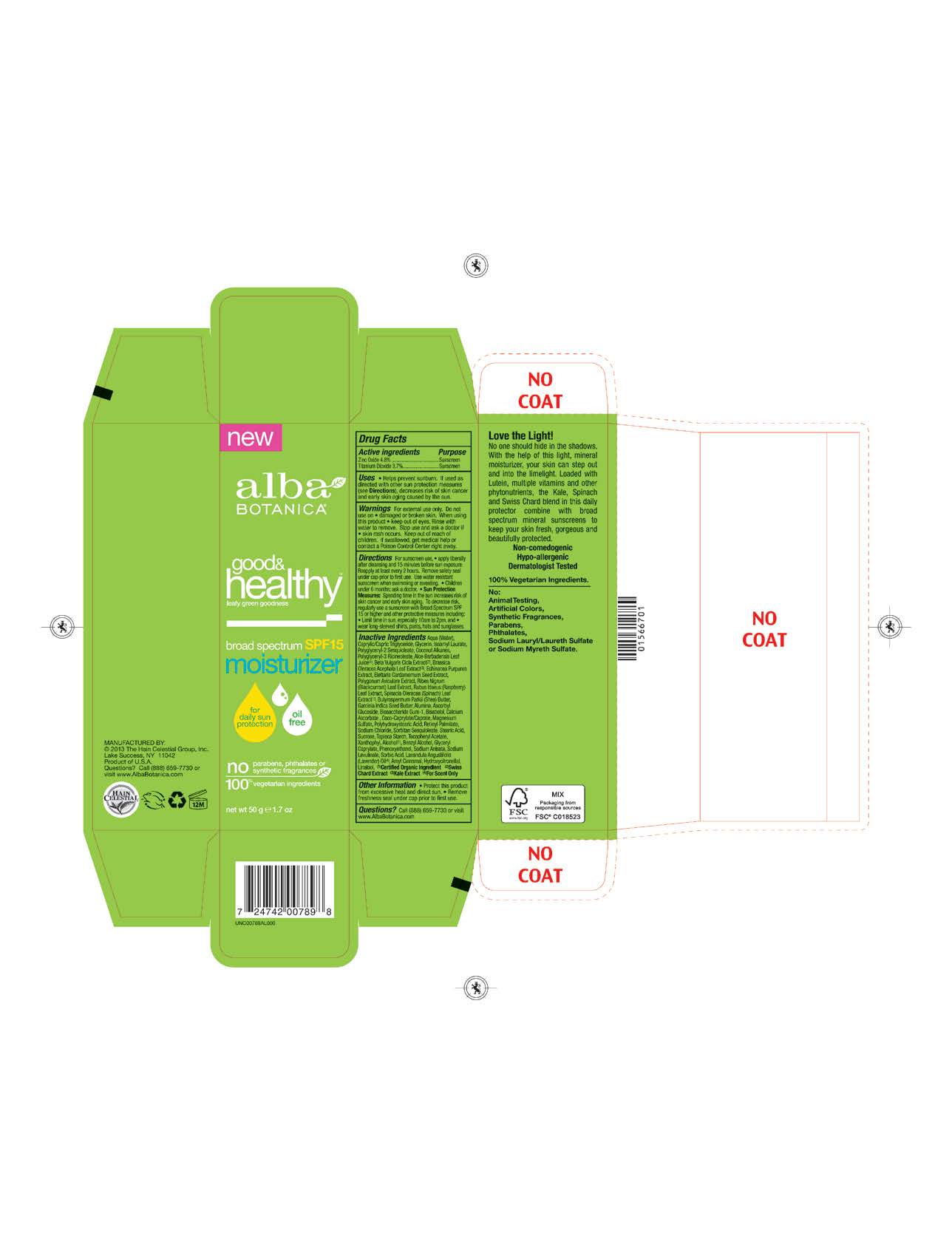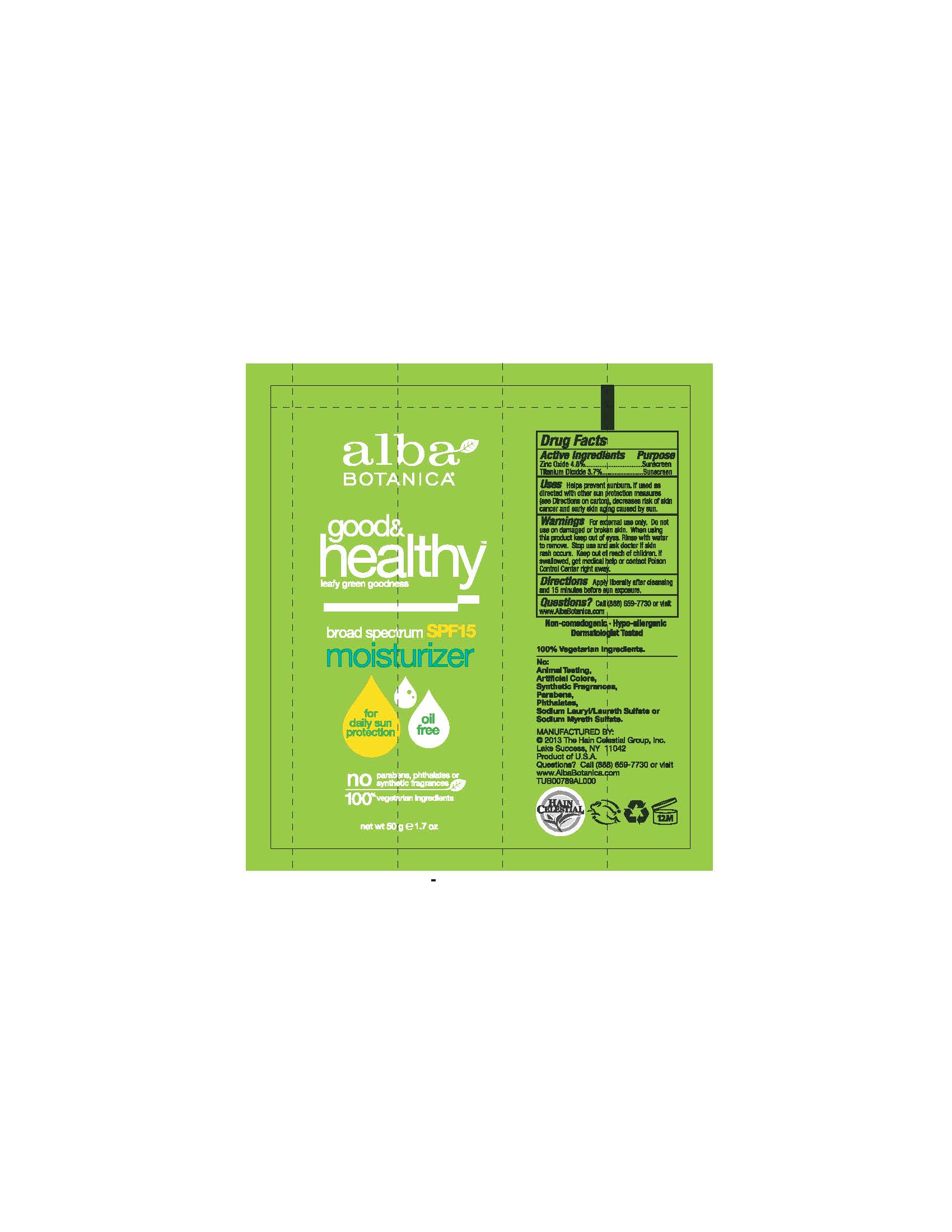 DRUG LABEL: Alba Good and Healthy Moisturizer SPF15
NDC: 61995-2789 | Form: CREAM
Manufacturer: The Hain Celestial Group, Inc.
Category: otc | Type: HUMAN OTC DRUG LABEL
Date: 20141029

ACTIVE INGREDIENTS: TITANIUM DIOXIDE 3.7 g/100 g; ZINC OXIDE 4.8 g/100 g
INACTIVE INGREDIENTS: RUBUS IDAEUS LEAF; RIBES NIGRUM LEAF; STARCH, TAPIOCA; CARDAMOM; ASCORBYL GLUCOSIDE; BIOSACCHARIDE GUM-1; LEVOMENOL; VITAMIN A PALMITATE; SUCROSE; LUTEIN; BETA VULGARIS; CALCIUM ASCORBATE; ALCOHOL; BENZYL ALCOHOL; PHENOXYETHANOL; ALOE VERA LEAF; ISOAMYL LAURATE; COCONUT ALKANES; GLYCERIN; POLYGLYCERYL-3 RICINOLEATE; WATER; SHEA BUTTER; ALUMINUM OXIDE; COCO-CAPRYLATE/CAPRATE; MAGNESIUM SULFATE; SODIUM CHLORIDE; SORBITAN SESQUIOLEATE; STEARIC ACID; ECHINACEA PURPUREA ROOT; POLYHYDROXYSTEARIC ACID (2300 MW); MEDIUM-CHAIN TRIGLYCERIDES; .ALPHA.-TOCOPHEROL ACETATE; GARCINIA INDICA SEED BUTTER; GLYCERYL CAPRYLATE; SORBIC ACID; KALE; SODIUM ANISATE; SODIUM LEVULINATE; LAVENDER OIL

Active Ingredient

Zinc Oxide 4.8%

Titanium Dioxide 3.7%

DOSAGE AND ADMINISTRATION

Cream.For sunscreen use apply liberall yafter cleansing and 15 minutes before sun exposure.Remove safety seal under cup prior to first use. Reapply at least every 2 hours. Use water resistant sunscreen when swimming or sweating

PURPOSE

Sunscreen

WARNINGS

For external use only. Do not use on damaged or broken skin. When using this product keep out of eyes. Rinse with water to remove. Stop use and ask a doctor if skin rash occurs.

Keep out of reach of children. If swallowed get medical help or contact Poison Center right away.

INACTIVE INGREDIENT

Water, Caprylic Capric Triglyceride,Glycerin, Isoamyl Laurate, Coconut Alkanes, Polyglyceryl-2 Sesquioleate, Polyglyceryl-3 Ricinoleate, Aloe Barbadensis Leaf Juice(1), Polyhydroxystearic Acid, Echinacea Purpurea Extract, Polygonum Aviculare Extract, Brassica Oleracea Acephala Leaf Extract, Elettaria Cardamomum Seed Extract, Ribes Nigrum (Blackcurrant) Leaf Extract, Rubus Idaeus (Raspberry) Leaf Extract, Spinacia Oleracea (Spinach) Leaf Extract, Garcinia Indica Seed Butter, Ascorbyl Glucoside, Biosaccharide Gum-1, Bisabolol, Retinyl Palmitate,Sucrose, Tapioca Starch,Lavandula Angusiofolia (Lavender) Oil, Tocopheryl Acetate, Butyrospermum Parkii (Shea) Butter, Beta Vulgaris (Beet)Root Extract, Alumina, Calcium Ascorbate, Coco-Caprylate/Caprate ,Xanthophyl,Glyceryl Caprylate, Magnesium Sulfate, Sodium Chloride, Sorbitan Sesquioleate, Stearic Acid, Alcohol (1), Benzyl Alcohol, Phenoxyethanol, Sodium Anisate, Sodium Lavulinate.

(1) Certified Organicf Ingredient

INDICATIONS AND USAGE

Helps prevents sunburns. If uses as directed with other sun protection measures, decreases risk of skin cancer and early skin aging caused by sun exposure. Skin Protection Measures: Spending time in the sun increases your risk of skin cancer and early skin aging. To decrease risk, regularly use sunscreen with Broad Spectrum SPF 15 or higher and other protective measures including: limit time in sun, especially from10am to 2pm, and wear long sleeved shirts, pants, hats and sunglases.